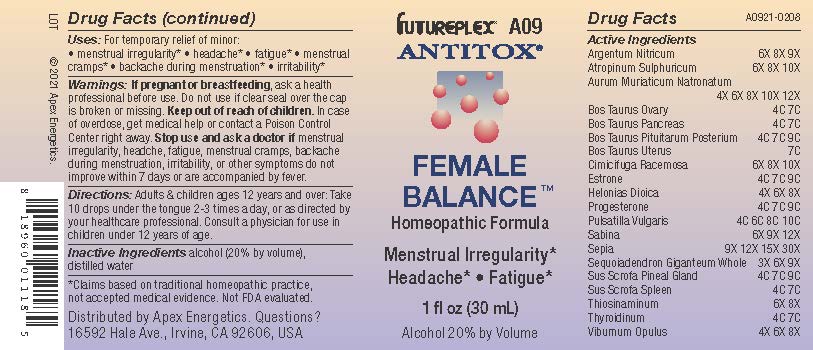 DRUG LABEL: A09
NDC: 63479-0109 | Form: SOLUTION/ DROPS
Manufacturer: Apex Energetics Inc.
Category: homeopathic | Type: HUMAN OTC DRUG LABEL
Date: 20240108

ACTIVE INGREDIENTS: JUNIPERUS SABINA LEAFY TWIG 12 [hp_X]/1 mL; SUS SCROFA SPLEEN 7 [hp_C]/1 mL; ALLYLTHIOUREA 8 [hp_X]/1 mL; THYROID, UNSPECIFIED 7 [hp_C]/1 mL; BOS TAURUS OVARY 7 [hp_C]/1 mL; BOS TAURUS PANCREAS 7 [hp_C]/1 mL; SILVER NITRATE 9 [hp_X]/1 mL; ESTRONE 9 [hp_C]/1 mL; SEPIA OFFICINALIS JUICE 30 [hp_X]/1 mL; SUS SCROFA PINEAL GLAND 9 [hp_C]/1 mL; CHAMAELIRIUM LUTEUM ROOT 8 [hp_X]/1 mL; PROGESTERONE 9 [hp_C]/1 mL; SEQUOIADENDRON GIGANTEUM WHOLE 9 [hp_X]/1 mL; VIBURNUM OPULUS BARK 8 [hp_X]/1 mL; ATROPINE SULFATE 10 [hp_X]/1 mL; SODIUM TETRACHLOROAURATE 12 [hp_X]/1 mL; BOS TAURUS PITUITARY GLAND 9 [hp_C]/1 mL; BOS TAURUS UTERUS 7 [hp_C]/1 mL; BLACK COHOSH 10 [hp_X]/1 mL; PULSATILLA VULGARIS 10 [hp_C]/1 mL
INACTIVE INGREDIENTS: WATER; ALCOHOL

A09

Active Ingredients
Argentum Nitricum | 6X 8X 9X
Atropinum Sulphuricum | 6X 8X 10X
Aurum Muriaticum Natronatum | 4X 6X 8X 10X 12X
Bos Taurus Ovary | 4C 7C
Bos Taurus Pancreas | 4C 7C
Bos Taurus Pituitarum Posterium | 4C 7C 9C
Bos Taurus Uterus | 7C
Cimicifuga Racemosa | 6X 8X 10X
Estrone | 4C 7C 9C
Helonias Dioica | 4X 6X 8X
Progesterone | 4C 7C 9C
Pulsatilla Vulgaris | 4C 6C 8C 10C
Sabina | 6X 9X 12X
Sepia | 9X 12X 15X 30X
Sequoiadendron Giganteum Whole | 3X 6X 9X
Sus Scrofa Pineal Gland | 4C 7C 9C
Sus Scrofa Spleen | 4C 7C
Thiosinaminum | 6X 8X
Thyroidinum | 4C 7C
Viburnum Opulus | 4X 6X 8X

INDICATIONS AND USAGE

Uses:

For temporary relief of minor:
• menstrual irregularity*

• headache*

• fatigue*

• menstrual cramps*

• backache during menstruation*

• irritability*

*Claims based on traditional homeopathic practice, not accepted medical evidence. Not FDA evaluated.

Warnings:

PREGNANCY OR BREAST FEEDING

If pregnant or breastfeeding, ask a health professional before use.

Do not use if clear seal over the cap is broken or missing.

Keep out of reach of children. In case of overdose, get medical help or contact a Poison Control Center right away.

Stop use and ask a doctor if menstrual irregularity, headche, fatigue, menstrual cramps, backache during menstruation, irritability, or other symptoms do not improve within 7 days or are accompanied by fever.

DOSAGE AND ADMINISTRATION

Adults & children ages 12 years and over: Take 10 drops under the tongue 2-3 times a day, or as directed by your healthcare professional. Consult a physician for use in children under 12 years of age.

INACTIVE INGREDIENT

alcohol (20% by volume), distilled water

Distributed by Apex Energetics. Questions?

16592 Hale Ave., Irvine, CA 92606, USA

PACKAGE LABEL

FUTUREPLEX® A09

ANTITOX®

FEMALE BALANCE ™

Homeopathic Formula

Menstrual Irregularity*

Headache* • Fatigue*

Alcohol 20% by Volume

1 fl oz (30 mL)